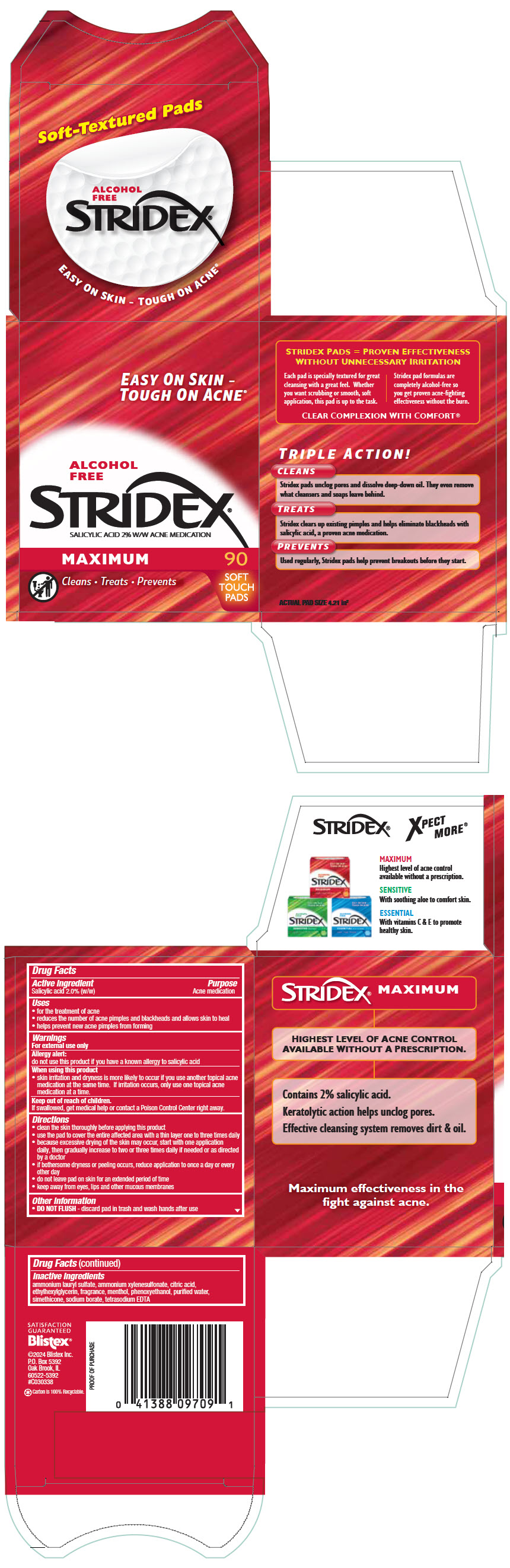 DRUG LABEL: Stridex 
NDC: 10157-1006 | Form: LIQUID
Manufacturer: Blistex Inc.
Category: otc | Type: HUMAN OTC DRUG LABEL
Date: 20241216

ACTIVE INGREDIENTS: SALICYLIC ACID 2 g/100 mL
INACTIVE INGREDIENTS: AMMONIUM LAURYL SULFATE; AMMONIUM XYLENESULFONATE; CITRIC ACID MONOHYDRATE; ETHYLHEXYLGLYCERIN; MENTHOL, UNSPECIFIED FORM; PHENOXYETHANOL; WATER; DIMETHICONOL/TRIMETHYLSILOXYSILICATE CROSSPOLYMER (40/60 W/W; 1000000 PA.S); SODIUM BORATE; EDETATE SODIUM

STRIDEX® MAXIMUM

Drug Facts

Active ingredient

Salicylic acid 2.0% (w/w)

Purpose

Acne medication

Uses

- for the treatment of acne
- reduces the number of acne pimples and blackheads and allows skin to heal
- helps prevent new acne pimples from forming

Warnings

For external use only

Allergy alert: do not use this product if you have a known allergy to salicylic acid

When using this product

- skin irritation and dryness is more likely to occur if you use another topical acne medication at the same time. If irritation occurs, only use one topical acne medication at a time.

Keep out of reach of children.

If swallowed, get medical help or contact a Poison Control Center right away.

Directions

- clean the skin thoroughly before applying this product
- use the pad to cover the entire affected area with a thin layer one to three times daily
- because excessive drying of the skin may occur, start with one application daily, then gradually increase to two or three times daily if needed or as directed by a doctor
- if bothersome dryness or peeling occurs, reduce application to once a day or every other day
- do not leave pad on skin for an extended period of time
- keep away from eyes, lips and other mucous membranes

Other information

- DO NOT FLUSH - discard pad in trash and wash hands after use

Inactive ingredients

ammonium lauryl sulfate, ammonium xylenesulfonate, citric acid, ethylhexylglycerin, fragrance, menthol, phenoxyethanol, purified water, simethicone, sodium borate, tetrasodium EDTA

PRINCIPAL DISPLAY PANEL - 90 Pad Jar Carton

EASY ON SKIN -
TOUGH ON ACNE®

ALCOHOL
FREE

STRIDEX®
SALICYLIC ACID 2% W/W ACNE MEDICATION

MAXIMUM

Cleans • Treats • Prevents

90
SOFT
TOUCH
PADS